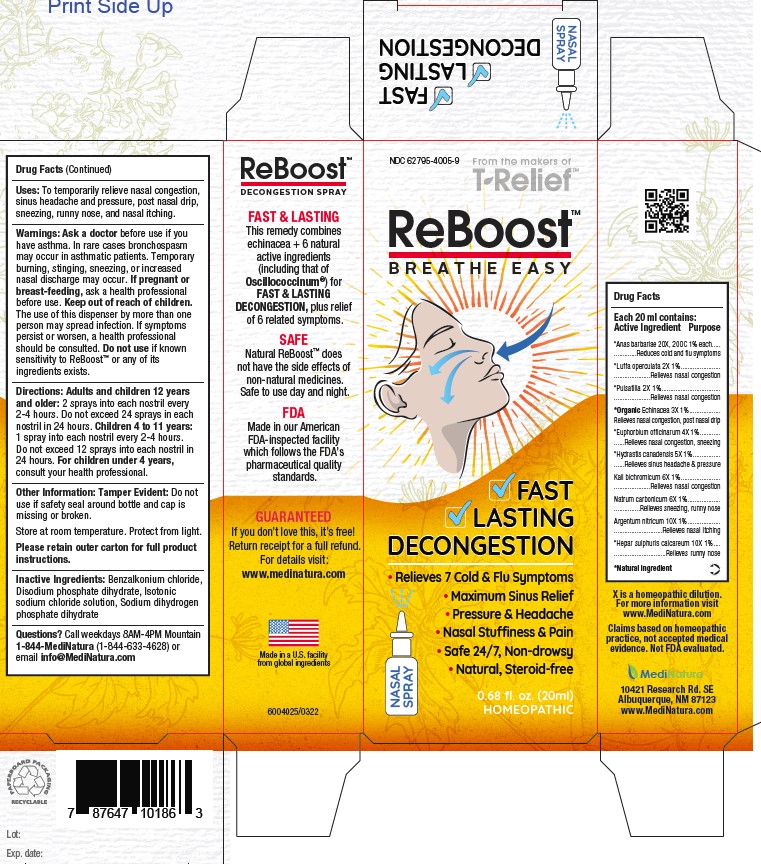 DRUG LABEL: ReBoost
NDC: 62795-4005 | Form: SPRAY
Manufacturer: MediNatura
Category: homeopathic | Type: HUMAN OTC DRUG LABEL
Date: 20220719

ACTIVE INGREDIENTS: SILVER NITRATE 10 [hp_X]/20 mL; EUPHORBIA RESINIFERA RESIN 4 [hp_X]/20 mL; CALCIUM SULFIDE 10 [hp_X]/20 mL; GOLDENSEAL 5 [hp_X]/20 mL; POTASSIUM DICHROMATE 6 [hp_X]/20 mL; LUFFA OPERCULATA FRUIT 2 [hp_X]/20 mL; SODIUM CARBONATE 6 [hp_X]/20 mL; PULSATILLA VULGARIS 2 [hp_X]/20 mL; CAIRINA MOSCHATA HEART/LIVER AUTOLYSATE 20 [hp_X]/20 mL; ECHINACEA, UNSPECIFIED 3 [hp_X]/20 mL
INACTIVE INGREDIENTS: BENZALKONIUM CHLORIDE; SODIUM PHOSPHATE, DIBASIC, DIHYDRATE; ISOTONIC SODIUM CHLORIDE SOLUTION; SODIUM PHOSPHATE, MONOBASIC, DIHYDRATE

Reboost

ACTIVE INGREDIENTS

Anas barbariae 20X, 200C 1%
*Luffa operculata 2X 1%
*Pulsatilla 2X 1%
*Organic Echinacea 3X 1%
*Euphorbium officinarum 4X 1%
*Hydrastis canadensis 5X 1%
Kali bichromicum 6X 1%
Natrum carbonicum 6X 1%
Argentum nitricum 10X 1%
*Hepar sulphuris calcareum 10X 1%

PURPOSE

Relieves nasal congestion
Relieves post nasal drip
Relieves sneezing
Relieves sinus headache & pressure
Relieves runny nose
Relieves nasal itching

OTC - KEEP OUT OF REACH OF CHILDREN SECTION

KEEP OUT OF REACH OF CHILDREN SECTION

Uses

Uses: To temporarily relieve nasal congestion.
To reduce cold and flu symptoms such as
sinus headache & pressure.

WARNINGS

Warnings: Ask a doctor before use if you
have asthma. In rare cases bronchospasm
may occur in asthmatic patients. Temporary
burning, stinging, sneezing, or increased
nasal discharge may occur. If pregnant or
breast-feeding, ask a health professional
before use. Keep out of reach of children.
The use of this dispenser by more than one
person may spread infection. If symptoms
persist or worsen, a health professional
should be consulted. Do not use if known
sensitivity to ReBoost™ or any of its
ingredients exists.

DIRECTIONS

Directions: Adults and children 12 years
and older: 2 sprays into each nostril every
2-4 hours. Do not exceed 24 sprays in each
nostril in 24 hours. Children 4 to 11 years:
1 spray into each nostril every 2-4 hours.
Do not exceed 12 sprays into each nostril in
24 hours. For children under 4 years,
consult your health professional.

INACTIVE INGREDIENTS

Inactive Ingredients: Benzalkonium chloride,
Disodium phosphate dihydrate, Isotonic
sodium chloride solution, Sodium dihydrogen
phosphate dihydrate

PACKAGE LABEL

Add image transcription here...